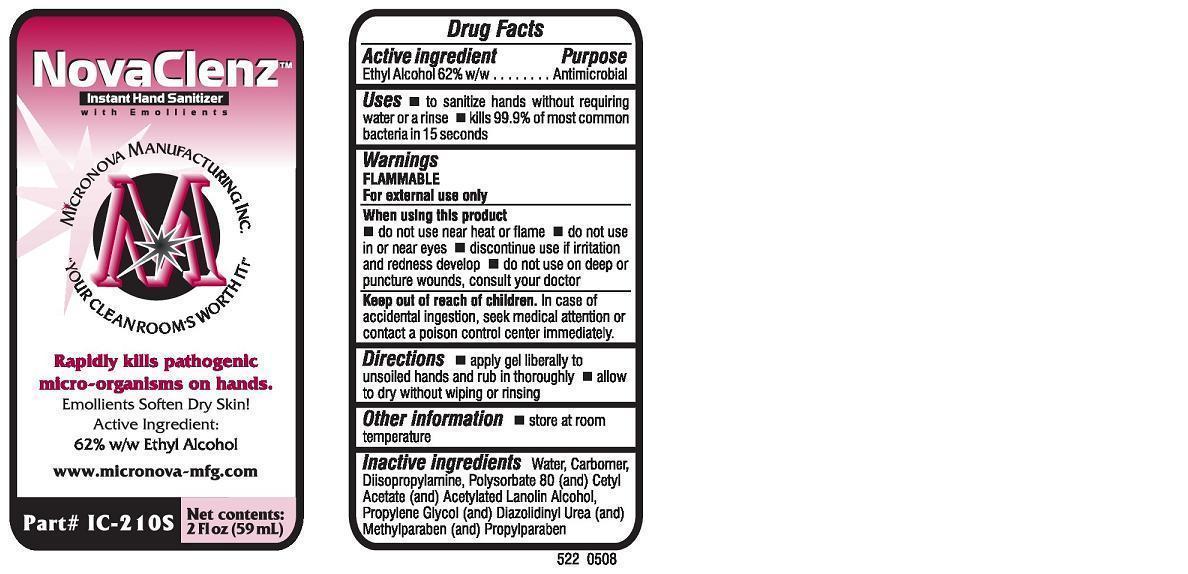 DRUG LABEL: NovaClenz Instant Hand Sanitizer
NDC: 59764-522 | Form: SOAP
Manufacturer: Micronova
Category: otc | Type: HUMAN OTC DRUG LABEL
Date: 20180207

ACTIVE INGREDIENTS: ALCOHOL 0.62 mL/1 mL
INACTIVE INGREDIENTS: WATER; CARBOMER HOMOPOLYMER TYPE C (ALLYL PENTAERYTHRITOL CROSSLINKED); POLYSORBATE 80; ACETYLATED LANOLIN ALCOHOLS; CETYL ACETATE; METHYLPARABEN; PROPYLPARABEN; DIAZOLIDINYL UREA; PROPYLENE GLYCOL; DIISOPROPYLAMINE

Active ingredient

Ethyl Alcohol 62 % w/w

Purpose

Antimicrobial

Keep out of reach of children

In case of accidental ingestion, seek medical attention or contact a poison control center immediately.

Uses

 to sanitize hands without requiring water or a rinse
 kills 99.9% of most common bacteria in 15 seconds

Warnings FLAMABLE For external use only

When using this product

 do not use near heat or flame

 do not use in or near eyes

 discontinue use if irritation and redness develop
 do not use on deep or punture wounds, consult your doctor

Directions

 apply gel liberally to unsoiled hands and rub in thoroughly  allow to dry without wiping or rinsing

Other information

 store at room temperature

Inactive ingredients:

Water, Carbomer, Diisopropylamine, Polysorbate 80 (and) Cetyl Acetate (and) Acetylated Lanolin Alcohol, Propylene Glycol (and) Diazolidinyl Urea (and) Methylparaben (and) Propylparaben